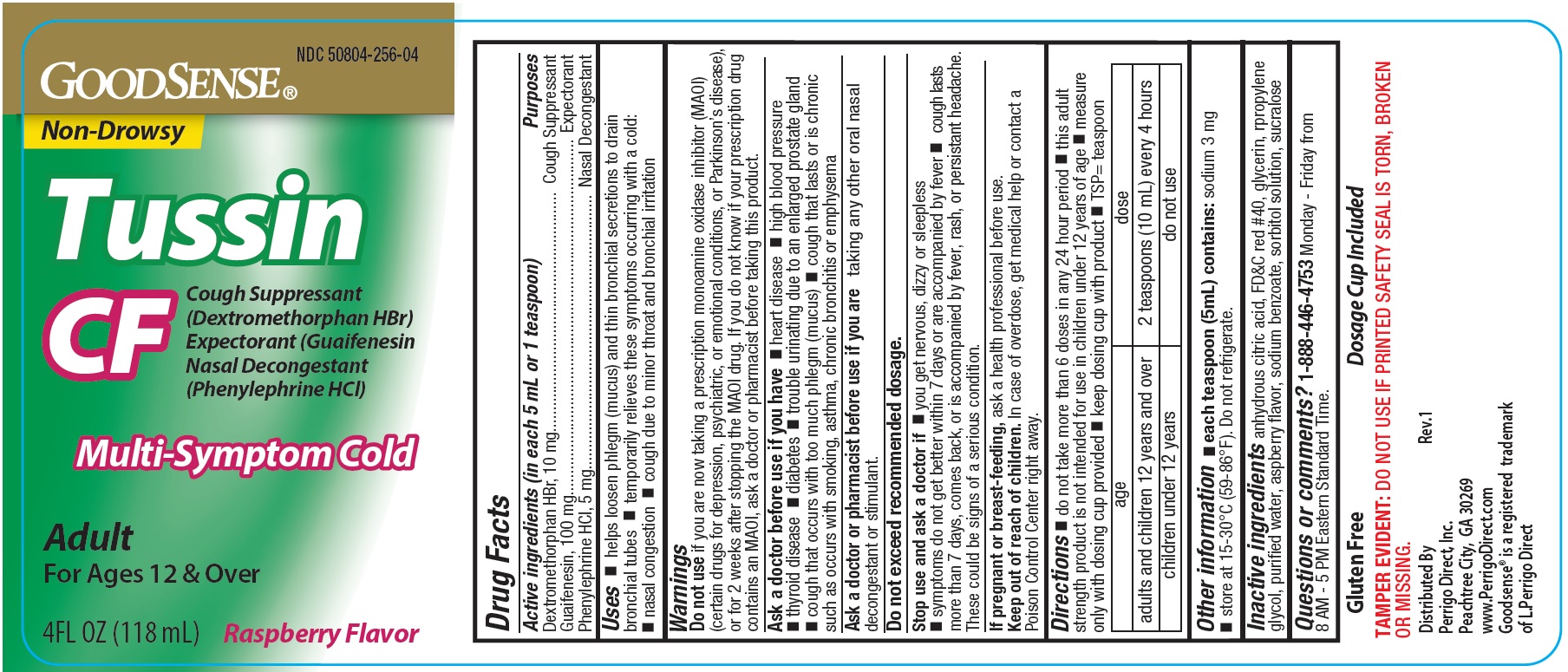 DRUG LABEL: GoodSense Tussin CF Multi-Symptom Cold, Raspberry
NDC: 50804-256 | Form: LIQUID
Manufacturer: Geiss, Destin & Dunn Inc.
Category: otc | Type: HUMAN OTC DRUG LABEL
Date: 20250917

ACTIVE INGREDIENTS: PHENYLEPHRINE HYDROCHLORIDE 5 mg/5 mL; DEXTROMETHORPHAN HYDROBROMIDE 10 mg/5 mL; GUAIFENESIN 100 mg/5 mL
INACTIVE INGREDIENTS: WATER; FD&C RED NO. 40; SORBITOL SOLUTION 70%; SUCRALOSE; GLYCERIN; SODIUM BENZOATE; ANHYDROUS CITRIC ACID; PROPYLENE GLYCOL

GoodSense Tussin CF Multi-Symptom Cold, Raspberry

ACTIVE INGREDIENT

Active ingredients (in each 5 mL or 1 teaspoon) Purposes
Dextromethorphan HBr, 10 mg........................................................ Cough Suppressant
Guaifenesin, 100 mg................................................................................... Expectorant
Phenylephrine HCI, 5 mg................................................................ Nasal Decongestant

Purposes
Cough Suppressant
Expectorant
Nasal Decongestant

Uses

• helps loosen phlegm (mucus) and thin bronchial secretions to drain bronchial tubes temporarily relieves these symptoms occurring with a cold:

• nasal congestion • cough due to minor throat and bronchial irritation

Warnings

Do not use if you are now taking a prescription monoamine oxidase inhibitor (MAOI)
(certain drugs for depression, psychiatric, or emotional conditions, or Parkinson’s disease),
or for 2 weeks after stopping the MAOI drug. If you do not know if your prescription drug
contains an MAOI, ask a doctor or pharmacist before taking this product.

Ask a doctor before use if you have • heart disease • high blood pressure
• thyroid disease • diabete s • trouble urinating due to an enlarged prostate gland
• cough that occurs with too much phlegm (mucus) • cough that lasts or is chronic
such as occurs with smoking, asthma, chronic bronchitis or emphysema

Ask a doctor or pharmacist before use if you are taking any other oral nasal
decongestant or stimulant.

OVERDOSAGE

Do not exceed recommended dosage.

Stop use and ask a doctor if • you get nervous, dizzy or sleepless
• symptoms do not get better within 7 days or are accompanied by fever • cough lasts
more than 7 days, comes back, or is accompanied by fever, rash, or persistant headache.
These could be signs of a serious condition.

PREGNANCY OR BREAST FEEDING

If pregnant or breast-feeding, ask a health professional before use.

Keep out of reach of children. In case of overdose, get medical help or contact a
Poison Control Center right away.

DOSAGE AND ADMINISTRATION

Directions • do not take more than 6 doses in any 24 hour period • this adult
strength product is not intended for use in children under 12 years of age • measure
only with dosing cup provided • keep dosing cup with product • TSP= teaspoon

age | dose
adults and children 12 years and over | 2 teaspoons (10 mL) every 4 hours
children under 12 years | do not use

Other information
• each teaspoon (5mL) contains: sodium 3 mg
• store at 15-30°C (59-86°F). Do not refrigerate.

INACTIVE INGREDIENT

Inactive ingredients anhydrous citric acid, FD&C red #40, glycerin, propylene
glycol, purified water, raspberry flavor, sodium benzoate, sorbitol solution, sucralose

Questions or comments? 1-888-446-4753 Monday - Friday from
8 AM - 5 PM Eastern Standard Time.